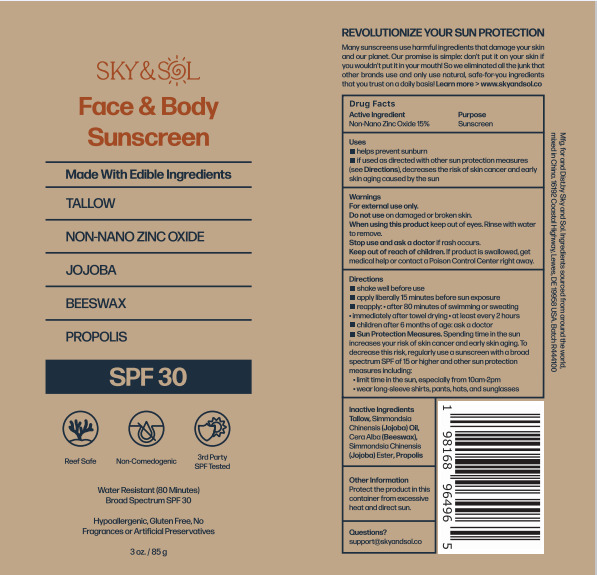 DRUG LABEL: Sky and Sol Sunscreen SPF30
NDC: 83447-007 | Form: CREAM
Manufacturer: Guangzhou Fantesy Biotechnology Co.,Ltd
Category: otc | Type: HUMAN OTC DRUG LABEL
Date: 20260105

ACTIVE INGREDIENTS: ZINC OXIDE 15 g/100 g
INACTIVE INGREDIENTS: BEEF TALLOW; JOJOBA OIL; YELLOW WAX; PROPOLIS WAX

83447-007

ACTIVE INGREDIENT

Zinc Oxide 15%

PURPOSE

sunscreen

Uses

■helps prevent sunburn
■if used as directed with other sun protection measures (see Directions), decreases the risk of skin cancer and early
skin aging caused by the sun

Warnings

①For external use only. ②Do not use on damaged or broken skin. ③When using this product keep out of eyes. Rinse with water to remove. ④Stop use and ask a doctor if rash occurs. ⑤Keep out of reach of children. If product is swallowed, get medical help or contact a Poison Control Center right away.

Do not use on damaged or broken skin.

Keep out of reach of children. If product is swallowed, get medical help or contact a Poison Control Center right away.

Directions

■ shake well before use
■ apply liberally 15 minutes before sun exposure
■ reapply: 1.after 80 minutes of swimming or sweating. 2. immediately after towel drying. 3.at least every 2 hours

■children after 6 months of age: ask a doctor
■Sun Protection Measures. Spending time in the sun increases your risk of skin cancer and early skin aging. To decrease this risk, regularlyuse a sunscreen with a broad spectrum SPF of 15 or higher and other sun protection measures including.
1. limit time in the sun, especially from 10am-2pm
2. wear long-sleeve shirts, pants, hats, and sunglasses

Other information

Protect the product in this container from excessive heat and direct sun

Inactive Ingredients

Tallow, Jojoba Oil, Beeswax, Propolis